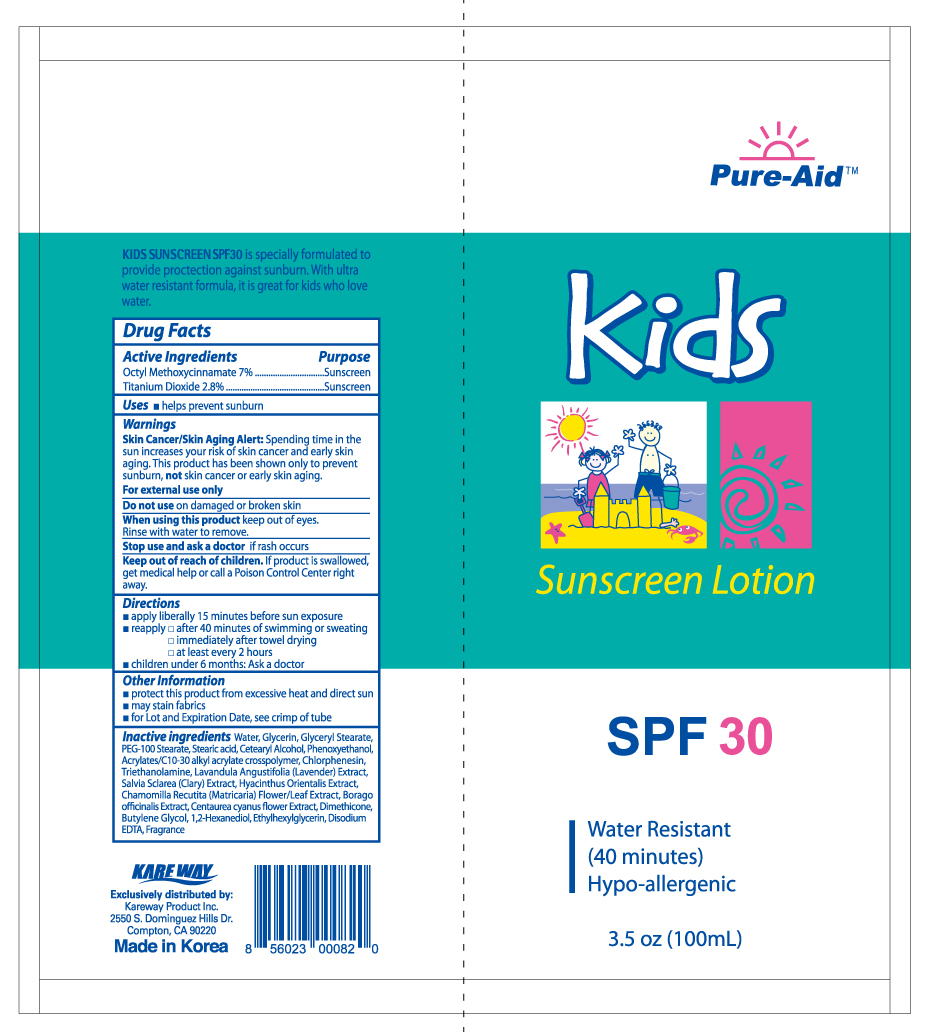 DRUG LABEL: Kids Sunscreen
NDC: 67510-0082 | Form: LOTION
Manufacturer: Kareway Product, Inc.
Category: otc | Type: HUMAN OTC DRUG LABEL
Date: 20191004

ACTIVE INGREDIENTS: OCTINOXATE 7 g/100 mL; TITANIUM DIOXIDE 2.8 g/100 mL
INACTIVE INGREDIENTS: GLYCERIN; GLYCERYL MONOSTEARATE; PEG-100 STEARATE; ETHYLHEXYLGLYCERIN; EDETATE DISODIUM ANHYDROUS; STEARIC ACID; TROLAMINE; WATER; 1,2-HEXANEDIOL; CARBOMER COPOLYMER TYPE A (ALLYL PENTAERYTHRITOL CROSSLINKED); CHLORPHENESIN; PHENOXYETHANOL; CETYL ALCOHOL; DIMETHICONE; BUTYLENE GLYCOL

Drug Facts

Active Ingredients

Octyl Methoxycinnamate 7%

Titanium Dioxide 2.8%

Purpose

Sunscreen

Sunscreen

Use

helps prevent sunburn

Warnings

Skin Cancer/Early Skin Aging Alert: Spending time in the sun increases your risk of skin cancer and early skin aging. This product has been shown only to prevent sunburn, not skin cancer or early skin aging.

For external use only.

Do not use

on damaged or broken skin

When using this product

Keep out of eyes. Rinse with water to remove.

Stop use and ask a doctor

if rash occurs

Keep out of reach of children.

If product is swallowed, get medical help or call a Poison Control Center right away.

Directions

- apply liberally 15 minutes before sun exposure
- reapply:
-
  - after 40 minutes of swimming or sweating
  - immediately after towel drying
  - at least every 2 hours
- children under 6 months: Ask a doctor

Other information

- protect this product from excessive heat and direct sun
- may stain fabrics
- for Lot and Expiration Date, see crimp of tube

Inactive Ingredients

Water, Glycerin, Glyceryl Stearate,

PEG-100 Stearate, Stearic acid, Cetearyl Alcohol, Phenoxyethanol,

Acrylates/C10-30 alkyl acrylate crosspolymer, Chlorphenesin,

Triethanolamine, Lavandula Angustifolia (Lavender) Extract,

Salvia Sclarea (Clary) Extract, Hyacinthus Orientalis Extract,

Chamomilla Recutita (Matricaria) Flower/Leaf Extract, Borago

officinalis Extract, Centaurea cyanus flower Extract, Dimethicone,

Butylene Glycol, 1,2-Hexanediol, Ethylhexylglycerin, Disodium

EDTA, Fragrance

Package label

Pure Aid Kids Sunscreen Lotion